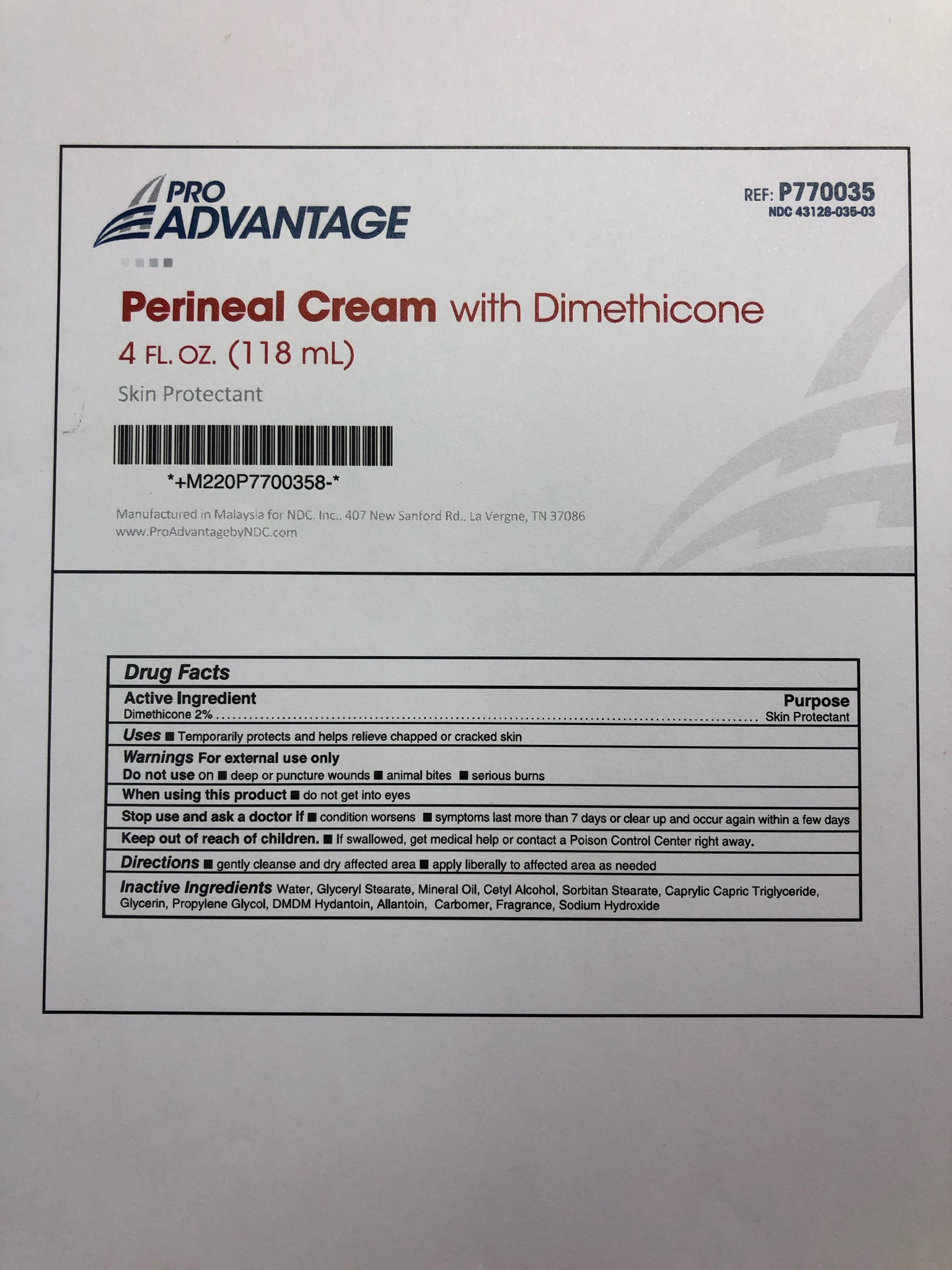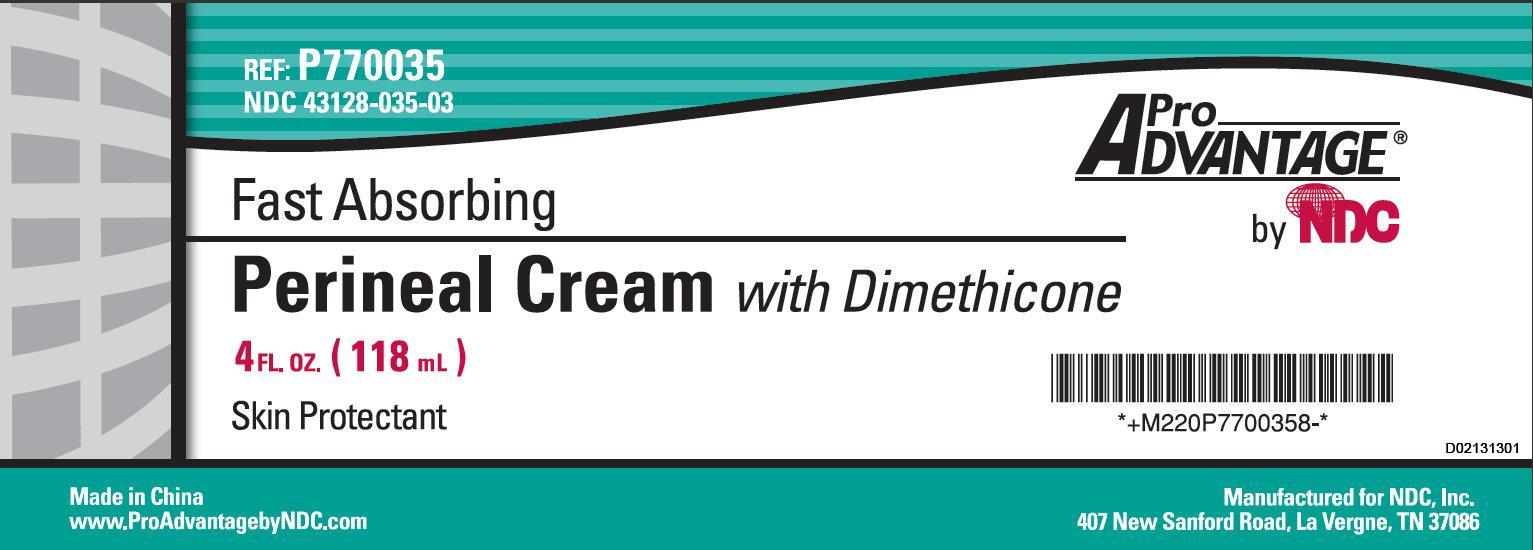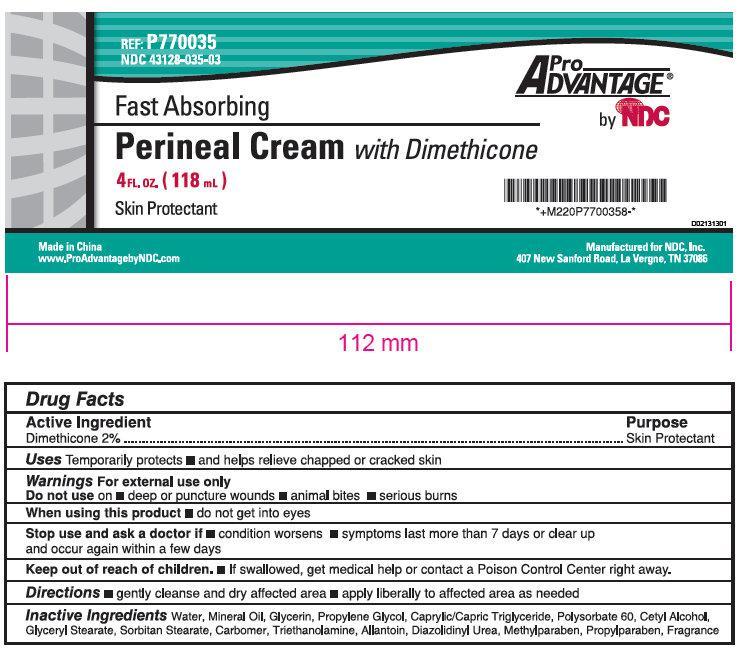 DRUG LABEL: Pro Advantage Fast Absorbing Perineal with Dimethicone Skin Protectant
NDC: 43128-035 | Form: CREAM
Manufacturer: NDC National Distribution & Contracting, Inc.
Category: otc | Type: HUMAN OTC DRUG LABEL
Date: 20190207

ACTIVE INGREDIENTS: DIMETHICONE 20 mg/1 mL
INACTIVE INGREDIENTS: WATER; MINERAL OIL; GLYCERIN; PROPYLENE GLYCOL; MEDIUM-CHAIN TRIGLYCERIDES; POLYSORBATE 60; CETYL ALCOHOL; GLYCERYL MONOSTEARATE; SORBITAN MONOSTEARATE; TROLAMINE; ALLANTOIN; DIAZOLIDINYL UREA; METHYLPARABEN; PROPYLPARABEN

Pro Advantage Fast Absorbing Perineal with Dimethicone Skin Protectant

Active Ingredient

Dimethicone 2%

Purpose

Skin Protectant

Uses

Temporarily protects • and helps relieve chapped or cracked skin

Warnings

For external use only

Do not use

on • deep or puncture wounds • animal bites • serious burns

When using this product

• do not get into eyes

Stop use and ask a doctor if

• condition worsens • symptoms last more than 7 days or clear up and occur again within a few days

Keep out of reach of children.

• If swallowed, get medical help or contact a Poison Control Center right away.

Directions:

• gently cleanse and dry affected area • apply liberally to affected area as needed.

Inactive Ingredients

Water, Mineral Oil, Glycerin, Propylene Glycol, Caprylic/Capric Triglyceride, Polysorbate 60, Cetyl Alcohol, Glyceryl Stearate, Sorbitan Stearate, Carbomer, Triethanolamine, Allantoin, Diazolidinyl Urea, Methylparaben, Propylparaben, Fragrance

REF: P770035 NDC 43128-035-03

Made in China
www.ProAdvantagebyNDC.com
Manufactured for NDC, Inc.
407 New Sanford Road, La Vergne, TN 37086

PACKAGE LABEL

Pro ADVANTAGE Fast Absorbing by NDC
Perineal Cream with Dimethicone
4FL.OZ (118 mL)
Skin Protectant